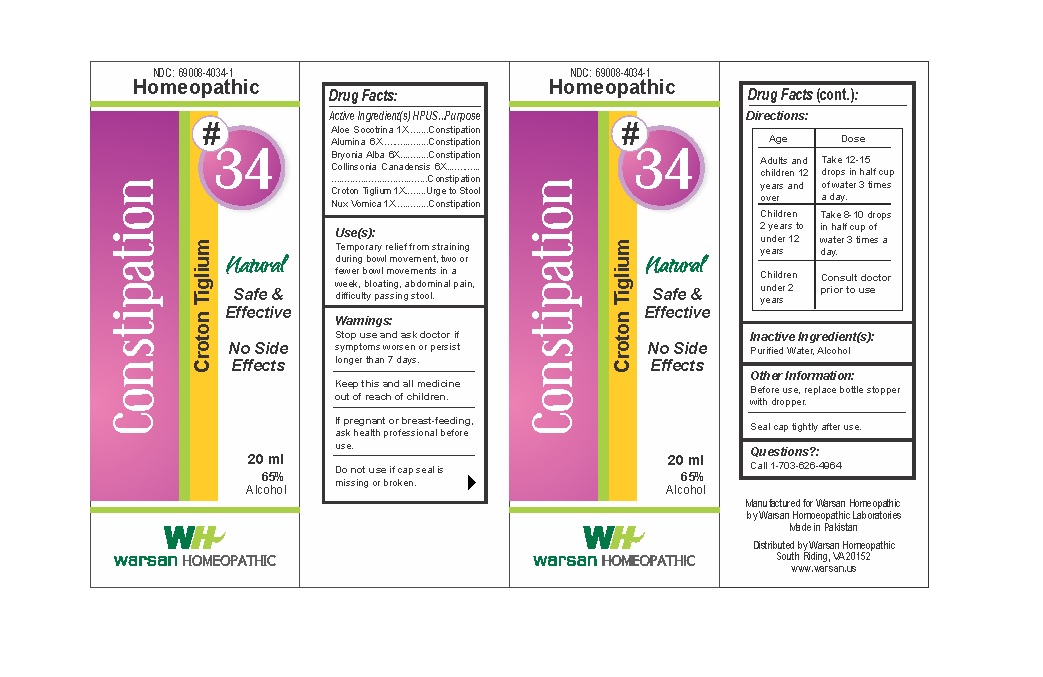 DRUG LABEL: Combination Remedy 34 - Constipation
NDC: 69008-4034 | Form: SOLUTION/ DROPS
Manufacturer: Warsan Homoeopathic Laboratories
Category: homeopathic | Type: HUMAN OTC DRUG LABEL
Date: 20171225

ACTIVE INGREDIENTS: BRYONIA ALBA ROOT 6 [hp_X]/1 mL; COLLINSONIA CANADENSIS ROOT 6 [hp_X]/1 mL; ALOE VERA LEAF 1 [hp_X]/1 mL; STRYCHNOS NUX-VOMICA SEED 1 [hp_X]/1 mL; ALUMINUM OXIDE 6 [hp_X]/1 mL; CROTON TIGLIUM SEED 1 [hp_X]/1 mL
INACTIVE INGREDIENTS: ALCOHOL; WATER

Stop use and ask doctor if symptoms worsen or persist longer than 7 days.

If pregnant or breast-feeding, ask health professional before use.

Do not use if tamper evident seal is missing or broken.

Keep out of reach of children.

ACTIVE INGREDIENT

Aloe Socotrina 1X

Alumina 6X

Bryonia Alba 6X

Collinsonia Canadensis 6X

Croton Tiglium 1X

Nux Vomica 1X

PURPOSE

Temporary relief from straining during bowl movement, two or fewer bowl movements in a week, bloating, abdominal pain,
difficulty passing stool.

INACTIVE INGREDIENT

Purified Water

Alcohol

DOSAGE AND ADMINISTRATION

Adults and children 12 years and older: Take 10-15 drops in half cup of water 3 times a day.

Children 2 years to under 12 years: Take 8-10 drops in half cup of water of 3 times a day.

Children under 2 years: Consult doctor prior to use.

INDICATIONS AND USAGE

Temporary relief from straining during bowl movement, two or fewer bowl movements in a week, bloating, abdominal pain,
difficulty passing stool.